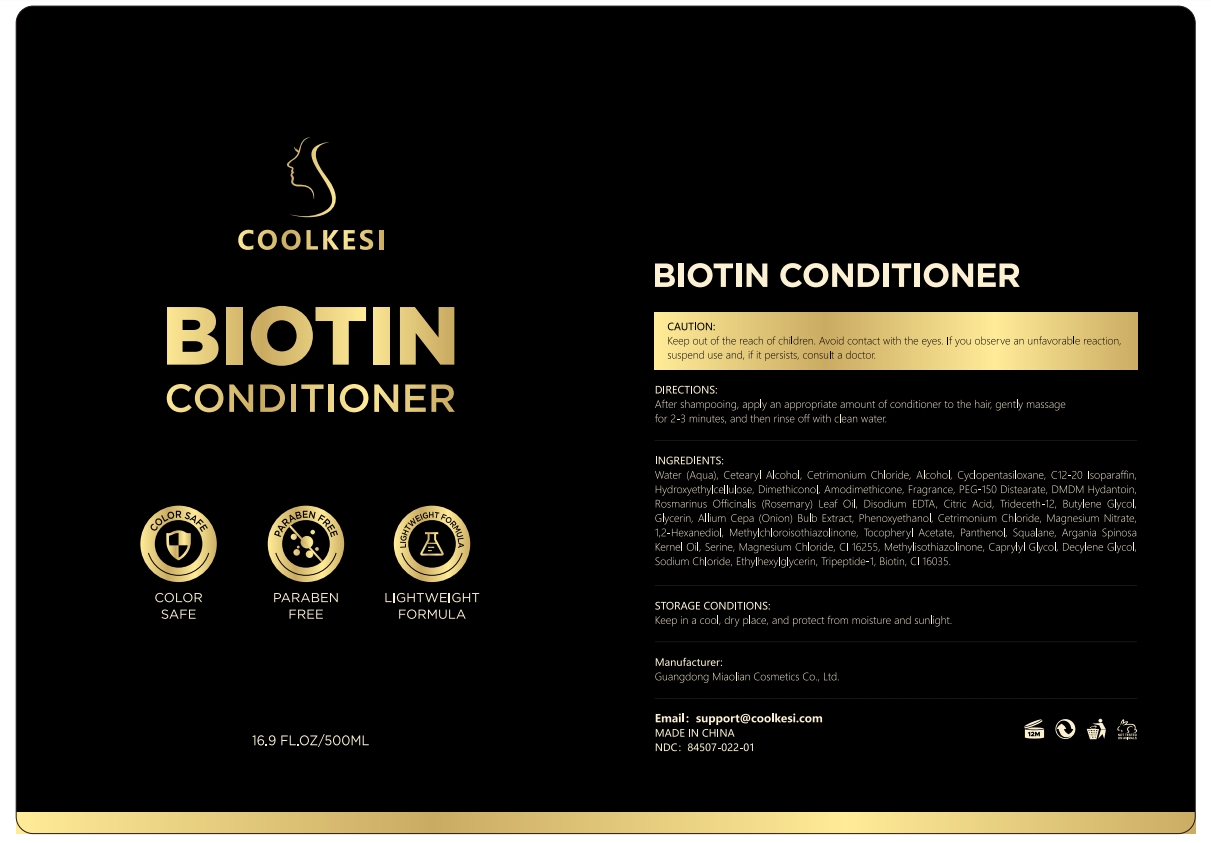 DRUG LABEL: COOLKESI BOTIN CONDITIONER
NDC: 84507-040 | Form: CREAM
Manufacturer: Guangdong Miaolian Cosmetics Co., Ltd.
Category: otc | Type: HUMAN OTC DRUG LABEL
Date: 20250611

ACTIVE INGREDIENTS: BUTYROSPERMUM PARKII (SHEA) BUTTER 0.1 mg/100 mL; MELALEUCA ALTERNIFOLIA (TEA TREE) LEAF OIL 0.1 mg/100 mL; VITIS VINIFERA (GRAPE) SEED OIL 0.1 mg/100 mL
INACTIVE INGREDIENTS: ETHYLHEXYLGLYCERIN; FRAGRANCE 13576; PHENOXYETHANOL; TOCOPHEROL; CETEARYL ALCOHOL; CITRIC ACID; PANTHENOL; GLYCERIN; STEARAMIDOPROPYL DIMETHYLAMINE; AMODIMETHICONE (240 CST); DIMETHICONOL (40 CST); ISOPROPYL PALMITATE; HYDROXYETHYLCELLULOSE; DIMETHICONE; SODIUM HYALURONATE; ARGANIA SPINOSA KERNEL OIL; BUTYLENE GLYCOL; HYDROLYZED WHEAT PROTEIN (ENZYMATIC, 3000 MW); WATER

DOSAGE AND ADMINISTRATION

After shampooing, apply an appropriate amount of conditioner to the hair gently massage - for 2-3 minutes, and then rinse off with clean water.

WARNINGS

Keep out of the reach of children. Avoid contact with the eyes. If you observe an unfavorable reaction, suspend use and, if it persists, consult a doctor.

INACTIVE INGREDIENT

WATER
GLYCERIN
CETEARYL ALCOHOL
STEARAMIDOPROPYL DIMETHYLAMINE
BIS-AMINOPROPYL DIMETHICONE
DIMETHICONE
ISOPROPYL PALMITATE
FRAGRANCE
CITRIC ACID
HYDROXYETHYLCELLULOSE
HYDROLYZED KERATIN
ARGANIA SPINOSA KERNEL OIL
PANTHENOL
TOCOPHEROL
SODIUM HYALURONATE
METHICONE
BUTYLENE GLYCOL
HYDROLYZED WHEAT PROTEIN
PHENOXYETHANOL
ETHYLHEXYLGLYCERIN

INDICATIONS AND USAGE

Deeply moisturizes hair. When used with Biotin Shampoo, it helps improve dryness, repair damage,and reduce split ends and breakage.

Keep out of the reach of children.

PURPOSE

Deeply moisturizes hair.

ACTIVE INGREDIENT

MELALEUCA ALTERNIFOLIA (TEA TREE) LEAF OIL-----0.1%
BUTYROSPERMUM PARKII (SHEA) BUTTER-----0.1%
VITIS VINIFERA (GRAPE) SEED OIL-----0.1%